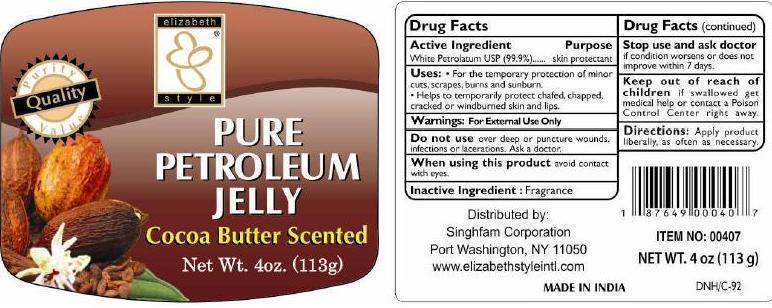 DRUG LABEL: Pure Petroleum Cocoa Butter Scented
NDC: 52920-125 | Form: JELLY
Manufacturer: Singhfam Corporation.
Category: otc | Type: HUMAN OTC DRUG LABEL
Date: 20121001

ACTIVE INGREDIENTS: PETROLATUM 0.99 g/1 g

PURE PETROLEUM JELLY COCOA BUTTER SCENTED

Active ingredient

White petrolatum USP (99.9 %)

Purpose

Skin protectant

Uses

- For the temporary protection of minor cuts, scrapes, burns and sunburn
- Helps to temporarily protect chafed, chapped, cracked or windburned skin and lips

Warnings

For external use only.

Do not use over deep or puncture wounds, infections or lacerations. Ask a doctor.

When using this product avoid contact with eyes.

Stop use and ask doctor if condition worsens or does not improve within 7 days.

Keep out of reach of children if swallowed get medical help or contact a Poison Control Center right away.

Directions

Apply liberally, as often as necessary.

Inactive ingredients

Fragrance

PRINCIPAL DISPLAY PANEL

PURE PETROLEUM JELLY

COCOA BUTTER SCENTED

NET WT. 4 OZ (113 g)